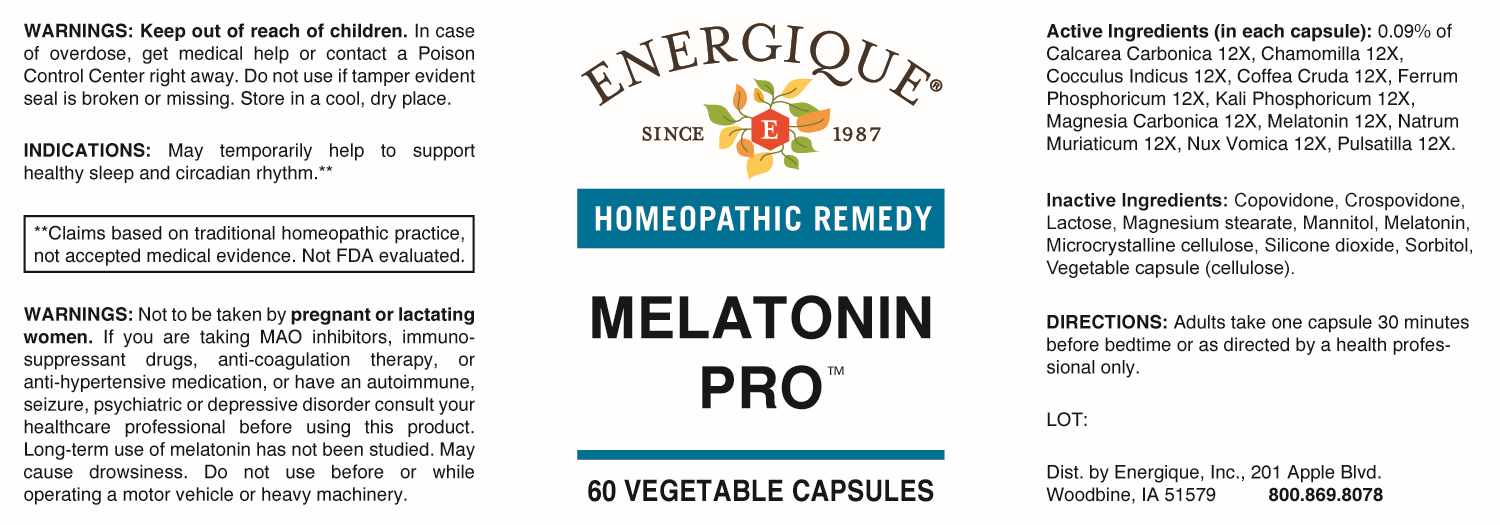 DRUG LABEL: Melatonin Pro
NDC: 44911-0500 | Form: TABLET
Manufacturer: Energique, Inc.
Category: homeopathic | Type: HUMAN OTC DRUG LABEL
Date: 20230719

ACTIVE INGREDIENTS: OYSTER SHELL CALCIUM CARBONATE, CRUDE 12 [hp_X]/1 1; MATRICARIA CHAMOMILLA 12 [hp_X]/1 1; ANAMIRTA COCCULUS SEED 12 [hp_X]/1 1; ARABICA COFFEE BEAN 12 [hp_X]/1 1; FERROSOFERRIC PHOSPHATE 12 [hp_X]/1 1; DIBASIC POTASSIUM PHOSPHATE 12 [hp_X]/1 1; MAGNESIUM CARBONATE 12 [hp_X]/1 1; MELATONIN 12 [hp_X]/1 1; SODIUM CHLORIDE 12 [hp_X]/1 1; STRYCHNOS NUX-VOMICA SEED 12 [hp_X]/1 1; PULSATILLA PRATENSIS WHOLE 12 [hp_X]/1 1
INACTIVE INGREDIENTS: SORBITOL; SILICON DIOXIDE; COPOVIDONE K25-31; CROSPOVIDONE, UNSPECIFIED; MANNITOL; MICROCRYSTALLINE CELLULOSE; ANHYDROUS LACTOSE; MAGNESIUM STEARATE; POWDERED CELLULOSE

DRUG FACTS:

ACTIVE INGREDIENTS:

(in each capsule): 0.09% of Calcarea Carbonica 12X, Chamomilla 12X, Cocculus Indicus 12X, Coffea Cruda 12X, Ferrum Phosphoricum 12X, Kali Phosphoricum 12X, Magnesia Carbonica 12X, Melatonin 12X, Natrum Muriaticum 12X, Nux Vomica 12X, Pulsatilla (Pratensis) 12X.

INDICATIONS:

May temporarily help to support healthy sleep and circadian rhythm.**

**Claims based on traditional homeopathic practice, not accepted medical evidence. Not FDA evaluated.

WARNINGS:

Keep out of reach of children. In case of overdose, get medical help or contact a Poison Control Center right away.

Do not use if tamper evident seal is broken or missing. Store in a cool, dry place.

Not to be taken by pregnant or lactating women. If you are taking MAO inhibitors, immunosuppressant drugs, anti-coagulation therapy, or anti-hypertensive medication, or have an autoimmune, seizure, psychiatric or depressive disorder consult your healthcare professional before using this product. Long-term use of melatonin has not been studied. May cause drowsiness. Do not use before or while operating a motor vehicle or heavy machinery.

KEEP OUT OF REACH OF CHILDREN:

In case of overdose, get medical help or contact a Poison Control Center right away.

DIRECTIONS:

Adults take one capsule 30 minutes before bedtime or as directed by a health professional only.

INDICATIONS:

May temporarily help to support healthy sleep and circadian rhythm.**

**Claims based on traditional homeopathic practice, not accepted medical evidence. Not FDA evaluated.

INACTIVE INGREDIENTS:

Copovidone, Crospovidone, Lactose, Magnesium Stearate, Mannitol, Melatonin, Microcrystalline Cellulose, Silicone Dioxide, Sorbitol, Vegetable Capsule (Cellulose).

QUESTIONS:

Dist. by Energique, Inc.

201 Apple Blvd

Woodbine, IA 51579 800.869.8078

PACKAGE LABEL DISPLAY:

ENERGIQUE
SINCE 1987
HOMEOPATHIC REMEDY
MELATONIN

PRO
60 VEGETABLE CAPSULES